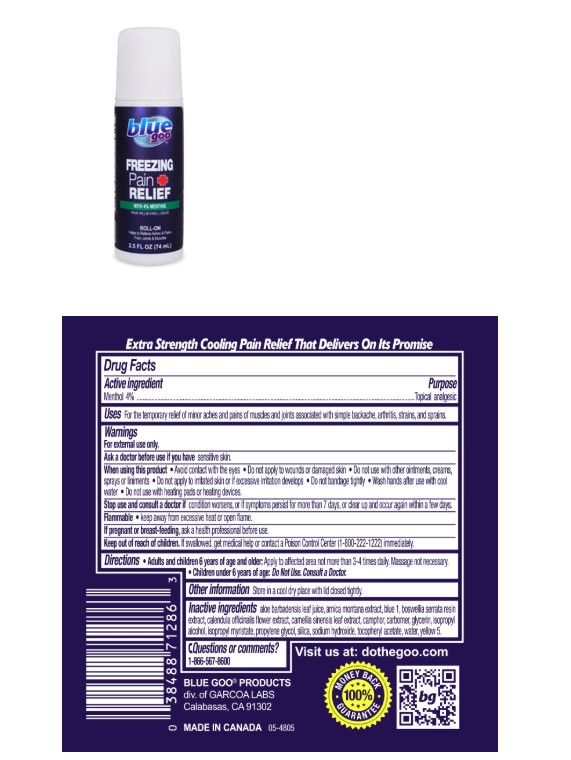 DRUG LABEL: blue goo FREEZING PAIN RELIEF
NDC: 67385-286 | Form: LIQUID
Manufacturer: Garcoa, Inc.
Category: otc | Type: HUMAN OTC DRUG LABEL
Date: 20260206

ACTIVE INGREDIENTS: MENTHOL 40 mg/1 mL
INACTIVE INGREDIENTS: ALOE BARBADENSIS LEAF JUICE; ARNICA MONTANA; BLUE 1; CALENDULA OFFICINALIS FLOWER; BOSWELLIA SERRATA RESIN OIL; CAMPHOR (SYNTHETIC); CAMELLIA SINENSIS LEAF; CARBOMER; GLYCERIN; ISOPROPYL ALCOHOL; ISOPROPYL MYRISTATE; PROPYLENE GLYCOL; SILICA; SODIUM HYDROXIDE; TOCOPHEROL; WATER; YELLOW 5

blue goo NERVE Pain RELIEF PAIN RELIEVING LIQUID

Active ingredient(s)

Menthol 4%

Purpose

Topical analgesic

Use(s)

Use for the temporary relief of minor aches and pains of muscles and joints associated with simple backache, arthritis, strains, and sprains.

Warnings

For external use only.

Ask a doctor if you have sensitive skin.

When using this product • Avoid contact with the eyes • Do not apply to wounds or damaged skin • Do not use with other ointments, creams, sprays or liniments • Do not apply to irritated skin or if excessive irritation develops • Do not bandage tightly • Wash hands after use with cool water • Do not use with heating pads or heating devices.

Stop use and consult a doctor if • condition worsens, or if symptoms persist for more than 7 days or clear up and occur again within a few days

Flammable • keep away from fire or flame.

If pregnant or breast-feeding ask a health professional before use.

Keep out of reach of children. if swallowed, get medical help or contact a Poison Control Center (1-800-222-1222) immediately.

Directions

Directions Adults and children 6 years age and older: Apply to affected area not more than 3 -4 times daily. Massage not necessary. • Children under 6 years of age: Do Not Use. Consult a Doctor.

Inactive ingredients

Inactive ingredients Aloe Barbadensis Leaf Juice, Arnica Montana Flower Extract, Blue 1, Boswellia Serrata Resin Extract, Calendula Officinalis Flower Extract, Camellia Sinensis Leaf Extract, Camphor, Carbomer, Glycerin, Isopropyl Alcohol, Isopropyl Myristate, Silica, Sodium Hydroxide, Tocopheryl Acetate, Water, Yellow 5

Questions

Question or comments? 1-866-567-8600

BLUE GOO PRODUCTS

div. of GARCOA LABS

Calabasas, CA 91302

Principal Display Panel

blue goo

FREEZING

PAIN

RELIEF

WITH 4% MENTHOL

PAIN RELIEVING LIQUID

ROLL-ON

Helps to Relieve Aches & Pains

From Joints & Muscles

2.5 FL OZ (74mL)

Blue Goo